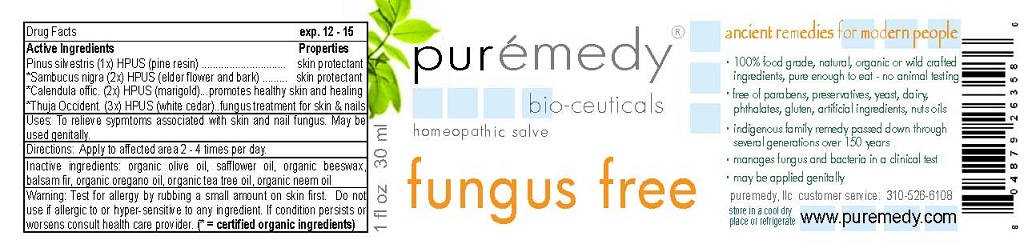 DRUG LABEL: FUNGUS FREE
NDC: 52810-501 | Form: SALVE
Manufacturer: PUREMEDY
Category: homeopathic | Type: HUMAN OTC DRUG LABEL
Date: 20240111

ACTIVE INGREDIENTS: SAMBUCUS NIGRA FLOWER 2 [hp_X]/100 mL; CALENDULA OFFICINALIS FLOWER 2 [hp_X]/100 mL; PINE NEEDLE OIL (PINUS SYLVESTRIS) 1 [hp_X]/100 mL; THUJA OCCIDENTALIS LEAFY TWIG 3 [hp_X]/100 mL
INACTIVE INGREDIENTS: OLIVE OIL; SAFFLOWER OIL; YELLOW WAX; CANADA BALSAM; OREGANO LEAF OIL; TEA TREE OIL; AZADIRACHTA INDICA SEED OIL

FUNGUS FREE (52810-501)

ACTIVE INGREDIENTS

PINUS SILVESTRIS (1X) HPUS (PINE RESIN)

*SAMBUCUS NIGRA (2X) HPUS (ELDER FLOWER AND BARK)

*CALENDULA OFFIC. (2X) HPUS) (MARIGOLD)

*THUJA OCCIDENT. (3X) HPUS (WHITE CEDAR)

PROPERTIES

SKIN PROTECTANT

SKIN PROTECTANT

PROMOTES HEALTHY SKIN AND HEALING

FUNGUS TREATMENT FOR SKIN AND NAILS

USES

TO RELIEVE SYMPTOMS ASSOCIATED WITH SKIN AND NAIL FUNGUS. MAY BE USED GENITALLY.

DIRECTIONS

APPLY TO AFFECTED AREA 2-4 TIMES PER DAY.

OTHER INGREDIENTS

ORGANIC OLIVE OIL, SAFFLOWER OIL, ORGANIC BEESWAX, BALSAM FIR, ORGANIC OREGANO OIL, ORGANIC TEA TREE OIL, ORGANIC NEEM OIL.

WARNING

TEST FOR ALLERGY BY RUBBING A SMALL AMOUNT ON SKIN FIRST. DO NOT USE IF ALLERGIC TO OR HYPER-SENSITIVE TO ANY INGREDIENT IN THIS SALVE. IF CONDITION PERSISTS OR WORSENS CONSULT YOUR HEALTH CARE PROVIDER. (* = CERTIFIED ORGANIC INGREDIENTS)

KEEP OUT OF REACH OF CHILDREN.

QUESTIONS

CUSTOMER SERVICE 310-526-6108

STORAGE AND HANDLING

STORE IN A COOL DRY PLACE OR REFRIGERATE